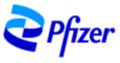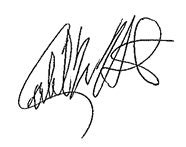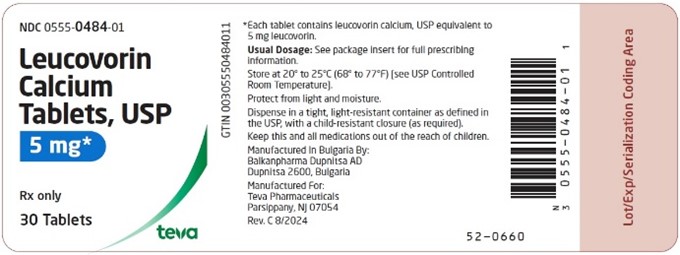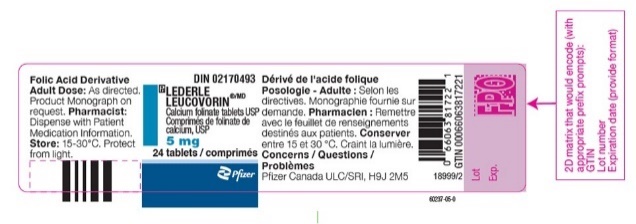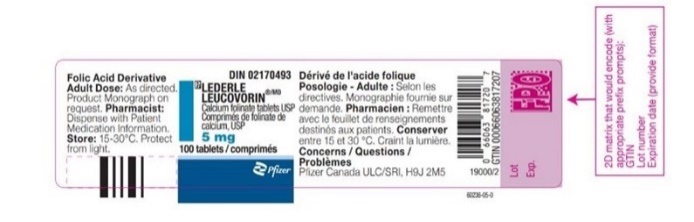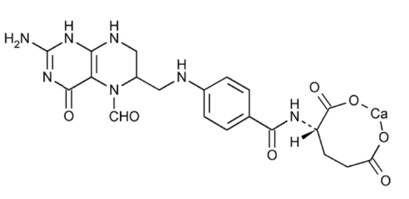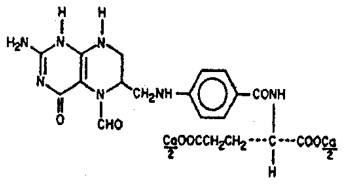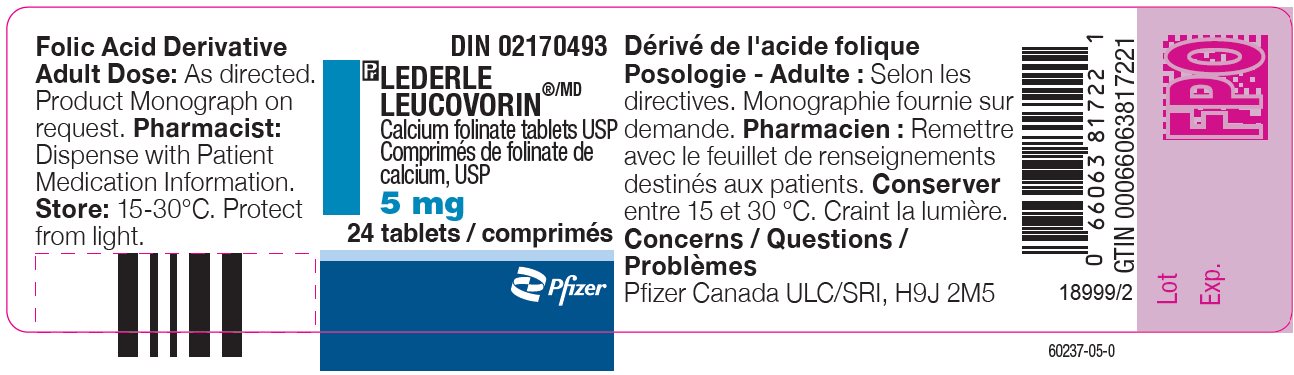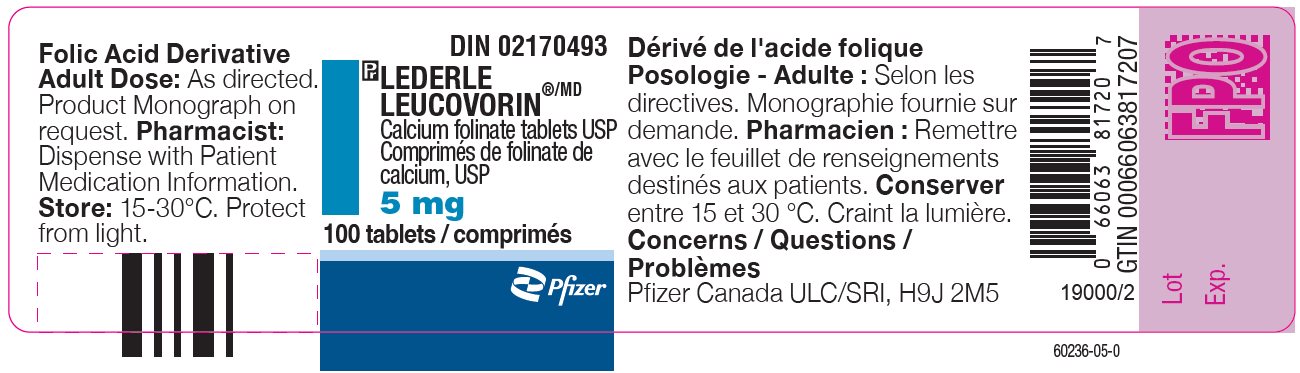 DRUG LABEL: LEDERLE LEUCOVORIN
NDC: 0069-5886 | Form: TABLET
Manufacturer: Pfizer Laboratories Div Pfizer Inc
Category: prescription | Type: HUMAN PRESCRIPTION DRUG LABEL
Date: 20251218

ACTIVE INGREDIENTS: LEUCOVORIN CALCIUM 5 mg/1 1
INACTIVE INGREDIENTS: MICROCRYSTALLINE CELLULOSE; LACTOSE MONOHYDRATE; SODIUM STARCH GLYCOLATE TYPE A; MAGNESIUM STEARATE; STARCH, CORN

LEUCOVORIN CALCIUM tablet

URGENT: Important Prescribing Information Letter

Subject:

Temporary Importation of Lederle Leucovorin® (Calcium Folinate tablets, USP) from Canada to Address U.S. Shortfall

December 2025

Dear Health Care Provider,

Due to the limited supply of Leucovorin Calcium tablets, USP in the United States (U.S.) market, Pfizer is coordinating at the request of the U.S. Food and Drug Administration (FDA) to temporarily import unapproved Lederle Leucovorin® (Calcium Folinate tablets, USP) 5 mg tablets marketed in Canada.

This product is manufactured by Pfizer’s Contract Manufacturer, Farmasierra, located in Madrid, Spain. The FDA has not approved Pfizer’s Lederle Leucovorin (Calcium Folinate tablets USP), 5 mg tablets in the U.S.; however, the FDA is permitting the temporary importation and distribution of this product. Leucovorin Calcium tablets, USP, is referred to as Calcium Folinate tablets, USP, outside of the U.S.

Effective immediately, and during this temporary period, Pfizer will distribute the following presentation(s) of unapproved Lederle Leucovorin® (Calcium Folinate, USP):

Product | Strength | Packaging | NDC | Batch | Expiration Date | Canada Marketing Authorization
Lederle Leucovorin®, Calcium Folinate, USP | 5 mg Tablet | 1x 24 Bottle | 0069-5886-24 | X773 | 04-30-2026 | Drug Identification Number (DIN) 02170493; Global Trade Item Number (GTIN) 066063817221
Lederle Leucovorin®, Calcium Folinate, USP | 5 mg Tablet | 1x 24 Bottle | 0069-5886-24 | X830 | 10-31-2026 | DIN 02170493; GTIN 066063817221
Lederle Leucovorin®, Calcium Folinate, USP | 5 mg Tablet | 1x 24 Bottle | 0069-5886-24 | Z361 | 03-31-2027 | DIN 02170493; GTIN 066063817221
Lederle Leucovorin®, Calcium Folinate, USP | 5 mg Tablet | 1x 100 Bottle | 0069-5886-99 | X831 | 10-31-2026 | DIN 02170493; GTIN 066063817207
Lederle Leucovorin®, Calcium Folinate, USP | 5 mg Tablet | 1x 100 Bottle | 0069-5886-99 | Z362 | 03-31-2027 | DIN 02170493; GTIN 066063817207

It is important to note that there are differences between the FDA-approved Leucovorin Calcium, USP products and the Calcium Folinate tablets, USP, marketed in Canada by Pfizer, Inc. Please see the product side-by-side label comparison table, where FDA-approved Leucovorin Calcium Tablets, USP 5 mg, manufactured by Teva Pharmaceuticals USA, Inc., is used as a reference.

It is important to note the following differences:

- Lederle Leucovorin® (Calcium Folinate tablets, USP) 5 mg tablets is indicated for diminishing the toxicity and counteracting the effect of impaired methotrexate elimination. Treatment of megaloblastic anemias due to folate deficiency, as in sprue, nutritional deficiency, megaloblastic anemias of pregnancy and infancy. FDA-approved Leucovorin Calcium, USP, product is contraindicated for pernicious anemia and other megaloblastic anemias caused by vitamin B12 deficiency.
- The container label will display the text used and approved for marketing Lederle Leucovorin® (Calcium Folinate tablets, USP) in Canada containing English and French text.
- Health Canada has not authorized an indication for pediatric use for the imported product. FDA-approved Leucovorin Calcium, USP, includes a specific warning in the Drug Interactions section regarding folic acid which in large amounts may counteract the antiepileptic effect of phenobarbital, phenytoin and primidone, and increase the frequency of seizures in susceptible children. The Canadian Product Monograph does not mention this specific age group (10-12).
- The Canadian Product Monograph includes a Post Marketing section addressing Adverse Drug Reactions, including that cases of Stevens-Johnson Syndrome (SJS) and Toxic Epidermal Necrolysis (TEN), some fatal, have been reported in patients receiving calcium folinate in combination with other agents known to be associated with these disorders. A contributory role of leucovorin in these occurrences of SJS/TEN cannot be excluded. Fatalities have occurred as a result of gastrointestinal toxicity (predominantly mucositis and diarrhea) and myelosuppression. In patients with diarrhea, rapid clinical deterioration leading to death can occur.
- The barcode of the imported product label may not register accurately on the U.S. scanning systems. Institutions should manually input the important product information into their systems and confirm that the barcode, if scanned, provides correct information. Alternative procedures should be followed to assure that the correct drug product is being used and administered to individual patients.
- The packaging of the imported product does not include serialization information. Pfizer’s Calcium Folinate, USP, marketed in Canada, does not meet the Drug Supply Chain Security (DSCSA) standards for Interoperable Exchange of Information for Tracing of Human, Finished Prescription Drugs. FDA has created an exemption for the product due to the limited supply.
- Leucovorin Calcium tablet, USP is available only by prescription in the U.S. However, the imported product does not have the statement “Rx only” on the labeling.

Please refer to the package insert for the FDA approved Leucovorin Calcium, USP, full Prescribing Information.

Adverse Events and Product Quality Complaints

To report adverse reactions or quality issues, contact Pfizer at 1-800-438-1985.

Adverse reactions or quality problems experienced with the use of this product may be reported to the FDA's MedWatch Adverse Event Reporting Program either online, by regular mail, or by fax:

- Complete and submit the report Online: www.fda.gov/medwatch/report.htm
- Regular mail or Fax: download form www.fda.gov/MedWatch/getforms.htm or call 1-800-332-1088 to request a reporting form, then complete and return to the address on the pre-addressed form, or submit by fax to 1-800-FDA-0178 (1-800-332-0178)
- When reporting, please indicate product is Lederle Leucovorin from Pfizer Canada and provide the lot number

Contact Information

Please contact Pfizer Customer Service at 1-800-533-4535 or dropships@pfizer.com (Mon.–Fri. 8am–5:30pm ET) or your Pfizer representative for any questions you may have regarding this notification.

Sincerely,

Pfizer Inc.

Caleb Hart

US PAVE Business Unit Lead

Side-by-Side Product Comparison of FDA-approved Leucovorin Calcium, USP, and Imported Product, Lederle Leucovorin Calcium Folinate, USP, Canada

US FDA APPROVED PRODUCT | IMPORTED PRODUCT
Product name
Leucovorin Calcium, USP (Teva) | LEDERLE LEUCOVORIN (PFIZER CANADA INC)
Dosage form and strength
5 mg tablet | 5 mg tablet
Container label
Description/Pharmaceutical information
DESCRIPTION; Leucovorin calcium tablets, USP contain either 5 mg or 25 mg leucovorin as the calcium salt of N-[4-[[(2-amino-5-formyl-1, 4, 5, 6, 7, 8-hexahydro-4-oxo-6-pteridinyl)methyl] amino]benzoyl]-L-glutamic acid. This is equivalent to 5.4 mg or 27.01 mg of anhydrous leucovorin calcium, respectively. In addition, each tablet contains the following inactive ingredients: colloidal silicon dioxide, croscarmellose sodium, lactose monohydrate, magnesium stearate, and microcrystalline cellulose. The 25 mg tablet also contains D&C yellow no. 10 aluminum lake and FD&C blue no. 1 aluminum lake. Leucovorin is a water soluble form of reduced folate in the folate group; it is useful as an antidote to drugs which act as folic acid antagonists. These tablets are intended for oral administration only. The structural formula is as follows:; C20 H21 CaN7 O7 M.W. 511.5 | SCIENTIFIC INFORMATION PHARMACEUTICAL INFORMATION Drug Substance Proper name: Leucovorin Calcium (folic acid derivative) is also known as calcium folinate, citrovorum factor, or the calcium salt of 5-formyl-5,6,7,8-tetrahydrofolic acid. Chemical name: L-Glutamic acid, N-[4[[(2-amino-5-formyl-1-4, 5, 6, 7, 8-hexahydro-4-oxo-6-pteridinyl) methyl] amino] benzoyl]-, calcium salt (l:l). Molecular formula and molecular mass: C20H21CaN7O7, 511.51 Structural formula:; Physicochemical properties: Leucovorin Calcium occurs as a yellowish white or yellow, odourless powder. It is sparingly soluble in water and practically insoluble in alcohol. It decomposes above 250°C. There is 0.004 mEq of calcium per mg of leucovorin in each tablet. MICROBIOLOGY No microbiological information is required for this drug product.
Clinical pharmacology
CLINICAL PHARMACOLOGY Leucovorin is a racemic mixture of the diastereoisomers of the 5-formyl derivative of tetrahydrofolic acid. The biologically active compound of the mixture is the (-)-L-isomer, known as Citrovorum factor, or (-)-folinic acid. Leucovorin does not require reduction by the enzyme dihydrofolate reductase in order to participate in reactions utilizing folates as a source of “one-carbon” moieties. Following oral administration, leucovorin is rapidly absorbed and enters the general body pool of reduced folates. The increase in plasma and serum folate activity (determined microbiologically with Lactobacillus casei) seen after oral administration of leucovorin is predominantly due to 5-methyltetrahydrofolate. Twenty normal men were given a single, oral 15 mg dose (7.5 mg/m^2) of leucovorin calcium and serum folate concentrations were assayed with L. casei. Mean values observed (± one standard error) were:; a) Time to peak serum folate concentration: 1.72 ± 0.08 hours, b) Peak serum folate concentration achieved: 268 ± 18 ng/mL, c) Serum folate half-disappearance time: 3.5 hours.; Oral tablets yielded areas under the serum folate concentration-time curves (AUCs) that were 12% greater than equal amounts of leucovorin given intramuscularly and equal to the same amounts given intravenously. Oral absorption of leucovorin is saturable at doses above 25 mg. The apparent bioavailability of leucovorin was 97% for 25 mg, 75% for 50 mg and 37% for 100 mg. | Clinical Studies/Pharmacodynamics Clinical Pharmacology Clinical Trials The clinical trial data on which the original indication was authorized is not available. 10.1 Mechanism of Action Calcium folinate, the calcium salt of folinic acid (citrovorum factor), is a mixture of the diastereoisomers of the 5-formyl derivative of tetrahydrofolic acid. The biologically active component of the mixture is the (-)-L-isomer. It is a metabolite of folic acid and an essential coenzyme for nucleic acid synthesis used in cytotoxic therapy. 10.2 Pharmacodynamics Calcium folinate is a reduced form of folic acid, which is readily converted to other reduced folic acid derivatives (e.g., tetrahydrofolate). Because it does not require reduction by dihydrofolate reductase as does folic acid, calcium folinate is not affected by blockage of this enzyme by folic acid antagonists (dihydrofolate reductase inhibitors). This allows purine and thymidine synthesis, and thus DNA, RNA and protein synthesis, to occur. Calcium folinate may limit methotrexate action on normal cells by competing with methotrexate for the same transport processes into the cell. Calcium folinate rescues bone marrow and gastrointestinal cells from methotrexate but has no apparent effect on pre-existing methotrexate nephrotoxicity. Calcium folinate is extensively converted to 5-methyltetrahydrofolate in the intestine prior to absorption. In this form, it is a major component of the total active human serum folate. Oral absorption is saturable at doses above 25 mg. Calcium folinate enhances the cytotoxicity of fluoropyrimidines such as 5-fluorouracil (5FU) by their metabolites, methylene tetrahydrofolate and fluorodeoxyuridine monophosphate, forming a stable ternary complex with thymidylate synthase and thereby decreasing intracellular levels of that enzyme and the product thymidylate. The cell then dies as a result of thymine starvation.
Indications and usage
INDICATIONS AND USAGE Leucovorin calcium tablets are indicated to diminish the toxicity and counteract the effects of impaired methotrexate elimination and of inadvertent overdosages of folic acid antagonists. | Indications & Usage LEDERLE LEUCOVORIN (calcium folinate) is indicated for:; - diminishing the toxicity and counteracting the effect of impaired methotrexate elimination. - treatment of megaloblastic anemias due to folate deficiency, as in sprue, nutritional deficiency, megaloblastic anemias of pregnancy and infancy.
Contraindications
CONTRAINDICATIONS Leucovorin is improper therapy for pernicious anemia and other megaloblastic anemias secondary to the lack of vitamin B12. A hematologic remission may occur while neurologic manifestations continue to progress. | Contraindications Calcium folinate therapy is contraindicated in patients with:; - Known hypersensitivity to the active substance or to any of the excipients. For a complete listing, see DOSAGE FORMS, STRENGTHS, COMPOSITION AND PACKAGING. - Pernicious anemia or other megaloblastic anemias where Vitamin B12 is deficient. A hematologic remission may occur while neurologic manifestations continue to progress.
Warnings & Precautions
WARNINGS | Warnings & Precautions
In the treatment of accidental overdosage of folic acid antagonists, leucovorin should be administered as promptly as possible. As the time interval between antifolate administration (e.g., methotrexate) and leucovorin rescue increases, leucovorin’s effectiveness in counteracting hematologic toxicity decreases. Monitoring of the serum methotrexate concentration is essential in determining the optimal dose and duration of treatment with leucovorin. Delayed methotrexate excretion may be caused by a third space fluid accumulation (i.e., ascites, pleural effusion), renal insufficiency, or inadequate hydration. Under such circumstances, higher doses of leucovorin or prolonged administration may be indicated. Doses higher than those recommended for oral use must be given intravenously. Leucovorin may enhance the toxicity of fluorouracil. Deaths from severe enterocolitis, diarrhea, and dehydration have been reported in elderly patients receiving weekly leucovorin and fluorouracil.^1 Concomitant granulocytopenia and fever were present in some but not all of the patients. The concomitant use of leucovorin with trimethoprim-sulfamethoxazole for the acute treatment of Pneumocystis carinii pneumonia in patients with HIV infection was associated with increased rates of treatment failure and mortality in a placebo-controlled study. |  | Serious Warnings and Precautions; - Calcium folinate should only be used with 5-fluorouracil or methotrexate under the direct supervision of a clinician experienced in the use of cancer chemotherapeutic agents. - Cases of Stevens - Johnson syndrome (SJS) and Toxic Epidermal Necrolysis (TEN), some fatal, have been reported in patients receiving calcium folinate in combination with other agents known to be associated with these disorders. - Fatalities have occurred as a result of gastrointestinal toxicity (particularly mucusitis and diarrhea) associated with calcium folinate use. - Fatalities have occurred as a result of myelosuppression associated with calcium folinate use. - Anaphylactoid/anaphylactic reactions (including shock) have occurred in patients administered calcium folinate.
PRECAUTIONS General Parenteral administration is preferable to oral dosing if there is a possibility that the patient may vomit or not absorb the leucovorin. Leucovorin has no effect on other established toxicities of methotrexate such as the nephrotoxicity resulting from drug and/or metabolite precipitation in the kidney. | Warnings And Precautions General; Since calcium folinate may enhance the toxicity of fluorouracil, calcium folinate /fluorouracil combination therapy for advanced colorectal cancer should be administered under the supervision of a physician experienced in the use of antimetabolite cancer chemotherapy. Particular care should be taken in the treatment of elderly or debilitated colorectal cancer patients (see 9 DRUG INTERACTIONS and 7.1.4 Geriatrics). Calcium folinate should only be used with 5-fluorouracil or methotrexate under the direct supervision of a clinician experienced in the use of cancer chemotherapeutic agents. Treatment-related deaths have been sporadically reported in patients treated with LEDERLE LEUCOVORIN plus fluorouracil combination therapy regimens. In general, diarrhea or stomatitis/mucositis are the first indications that severe and potentially life-threatening toxicity could develop. Patients who experience these symptoms while receiving any combination therapy regimen incorporating LEDERLE LEUCOVORIN plus fluorouracil should be carefully followed and further therapy should be withheld until these symptoms resolve. Gastrointestinal Gastrointestinal toxicities (particularly stomatitis and diarrhea) are observed more commonly and may be more severe in patients receiving LEDERLE LEUCOVORIN plus fluorouracil combination (see 9 DRUG INTERACTIONS, 9.2 Drug Interactions Overview). Therapy with LEDERLE LEUCOVORIN /fluorouracil must not be initiated or continued in patients who have symptoms of gastrointestinal toxicity of any severity, until those symptoms have resolved. Patients with diarrhea must be monitored with particular care until the diarrhea has resolved, as rapid clinical deterioration leading to death can occur. Elderly or debilitated patients are at greater risk for severe toxicity receiving this therapy. Hematologic LEDERLE LEUCOVORIN (calcium folinate) treatment may mask pernicious anemia and other megaloblastic anemias resulting from vitamin B12 deficiency. LEDERLE LEUCOVORIN should not be used for the treatment of macrocytosis caused by direct or indirect DNA synthesis inhibitors (e.g. hydroxycarbamide, cytarabine, mercaptopurine, thioguanine). Monitoring and Laboratory Tests The following provides general advice for monitoring patients; however, specific monitoring recommendations may vary with local medical practice. 5-fluorouracil/calcium folinate therapy Complete blood count (CBC) with differential and platelets: prior to each treatment; weekly during the first two courses; at time of anticipated white blood cell (WBC) nadir in all courses thereafter. Electrolytes and liver function tests: prior to each treatment for the first three courses and prior to every other course thereafter. Methotrexate/calcium folinate therapy Serum creatinine levels and serum methotrexate levels: at least once daily. Urine pH: in cases of methotrexate overdose or delayed excretion, monitor as appropriate, to ensure maintenance of pH ≥7.0. Neurologic Seizures and/or syncope have been reported rarely in cancer patients receiving calcium folinate, usually in association with fluoropyrimidine and anti-epileptic drugs such as phenobarbital, phenytoin, primidone, and succinimides administration (see 9 DRUG INTERACTIONS). In epileptic patients treated with phenobarbital, phenytoin, primidone, and succinimides there is a risk to increase the frequency of seizures due to a decrease of plasma concentrations of anti-epileptic drugs. Clinical monitoring, possibly monitoring of the plasma concentrations and, if necessary, dose adaptation of the anti-epileptic drug during calcium folinate administration and after discontinuation is recommended. Reproductive Health: Female and Male Potential Fertility LEDERLE LEUCOVORIN (calcium folinate) is an intermediate product in the metabolism of folic acid and occurs naturally in the body. No fertility studies have been conducted with calcium folinate in animals. Skin Cases of Stevens - Johnson syndrome (SJS) and Toxic Epidermal Necrolysis (TEN), some fatal, have been reported in patients receiving calcium folinate in combination with other agents known to be associated with these disorders. A contributory role of leucovorin in these occurrences of SJS/TEN cannot be excluded (see 3 SERIOUS WARNINGS AND PRECAUTIONS).
Drug Interactions
Drug Interactions Folic acid in large amounts may counteract the antiepileptic effect of phenobarbital, phenytoin and primidone, and increase the frequency of seizures in susceptible children. Preliminary animal and human studies have shown that small quantities of systemically administered leucovorin enter CSF primarily as 5-methyltetrahydrofolate and, in humans, remain 1 to 3 orders of magnitude lower than usual methotrexate concentrations following intrathecal administration. However, high doses of leucovorin may reduce the efficacy of intrathecally administered methotrexate. Leucovorin may enhance the toxicity of fluorouracil (see WARNINGS). | Serious Drug Interactions Serious Drug Interactions; - Treatment-related deaths have been sporadically reported in patients treated with LEDERLE LEUCOVORIN plus fluorouracil combination therapy regimens. In general, diarrhea or stomatitis/mucositis are the first indications that severe and potentially life-threatening toxicity could develop. Patients who experience these symptoms while receiving any combination therapy regimen incorporating LEDERLE LEUCOVORIN plus fluorouracil should be carefully followed and further therapy should be withheld until these symptoms resolve (see 9.4 Drug-Drug Interactions).; Drug Interactions Overview Calcium folinate may diminish the effect of anti-epileptic substances: phenobarbital, primidone, phenytoin and succinimides, and may increase the frequency of seizures (a decrease of plasma levels of enzymatic inductor anticonvulsant drugs may be observed because the hepatic metabolism is increased as folates are one of the cofactors). Seizures and/or syncope have been reported rarely in cancer patients receiving leucovorin, usually in association with fluoropyrimidine administration, and most commonly in those with CNS metastases or other predisposing factors; however, a causal relationship has not been established. In epileptic patients treated with phenobarbital, phenytoin, primidone, and succinimides there is a risk to increase the frequency of seizures due to a decrease of plasma concentrations of anti-epileptic drugs. Clinical monitoring, possibly monitoring of the plasma concentrations and, if necessary, dose adaptation of the anti-epileptic drug during calcium folinate administration and after discontinuation is recommended. When calcium folinate is given in conjunction with a folic acid antagonist (eg, cotrimoxazole, pyrimethamine, methotrexate, antibiotic with antifolic effect) the efficacy of the folic acid antagonist may either be reduced or completely neutralised. Preliminary animal and human studies have shown that small quantities of systemically administered LEDERLE LEUCOVORIN enter the CSF primarily as 5-methyltetrahydrofolate and, in humans, remain 1-3 orders of magnitude lower than the usual methotrexate concentrations following intrathecal administration. However, high doses of LEDERLE LEUCOVORIN may reduce the efficacy of intrathecally administered methotrexate. LEDERLE LEUCOVORIN may enhance the toxicity of fluorouracil (see 7 WARNINGS AND PRECAUTIONS). When these drugs are administered concurrently in the palliative therapy of advanced colorectal cancer, the dosage of fluorouracil must be reduced. Although the toxicities observed in patients treated with the combination of LEDERLE LEUCOVORIN plus fluorouracil are qualitatively similar to those observed in patients treated with fluorouracil alone, gastrointestinal toxicities (particularly stomatitis and diarrhea) are observed more commonly and may be more severe in patients receiving the combination (See 7 WARNINGS AND PRECAUTIONS). Drug-Behavioural Interactions Interactions with behaviour have not been established. Drug-Drug Interactions Table 4 - Established or Potential Drug-Drug Interactions
Drug Interactions Folic acid in large amounts may counteract the antiepileptic effect of phenobarbital, phenytoin and primidone, and increase the frequency of seizures in susceptible children. Preliminary animal and human studies have shown that small quantities of systemically administered leucovorin enter CSF primarily as 5-methyltetrahydrofolate and, in humans, remain 1 to 3 orders of magnitude lower than usual methotrexate concentrations following intrathecal administration. However, high doses of leucovorin may reduce the efficacy of intrathecally administered methotrexate. Leucovorin may enhance the toxicity of fluorouracil (see WARNINGS). | leucovorin |  |  | Source of Evidence |  | Effect |  | Clinical comment
Drug Interactions Folic acid in large amounts may counteract the antiepileptic effect of phenobarbital, phenytoin and primidone, and increase the frequency of seizures in susceptible children. Preliminary animal and human studies have shown that small quantities of systemically administered leucovorin enter CSF primarily as 5-methyltetrahydrofolate and, in humans, remain 1 to 3 orders of magnitude lower than usual methotrexate concentrations following intrathecal administration. However, high doses of leucovorin may reduce the efficacy of intrathecally administered methotrexate. Leucovorin may enhance the toxicity of fluorouracil (see WARNINGS). | Anticonvulsants (phenobarbital, primidone, phenytoin and succinimides) |  |  | T |  | Diminished effect |  | May increase the frequency of seizures
Drug Interactions Folic acid in large amounts may counteract the antiepileptic effect of phenobarbital, phenytoin and primidone, and increase the frequency of seizures in susceptible children. Preliminary animal and human studies have shown that small quantities of systemically administered leucovorin enter CSF primarily as 5-methyltetrahydrofolate and, in humans, remain 1 to 3 orders of magnitude lower than usual methotrexate concentrations following intrathecal administration. However, high doses of leucovorin may reduce the efficacy of intrathecally administered methotrexate. Leucovorin may enhance the toxicity of fluorouracil (see WARNINGS). | Folic acid antagonist (eg: cotrimoxazole, pyrimethamine, methotrexate, antibiotic with antifolic effect) |  |  | T |  | Diminished effect |  | Efficacy may be reduced or completely neutralized
Drug Interactions Folic acid in large amounts may counteract the antiepileptic effect of phenobarbital, phenytoin and primidone, and increase the frequency of seizures in susceptible children. Preliminary animal and human studies have shown that small quantities of systemically administered leucovorin enter CSF primarily as 5-methyltetrahydrofolate and, in humans, remain 1 to 3 orders of magnitude lower than usual methotrexate concentrations following intrathecal administration. However, high doses of leucovorin may reduce the efficacy of intrathecally administered methotrexate. Leucovorin may enhance the toxicity of fluorouracil (see WARNINGS). | Methotrexate |  |  | CT |  | Diminished effect |  | small quantities of systemically administered leucovorin enter the CSF primarily as 5-methyltetrahydrofolate and remain 1-3 orders of magnitude lower than the usual methotrexate concentrations following intrathecal administration. High doses of leucovorin may reduce the efficacy of intrathecally administered methotrexate
Drug Interactions Folic acid in large amounts may counteract the antiepileptic effect of phenobarbital, phenytoin and primidone, and increase the frequency of seizures in susceptible children. Preliminary animal and human studies have shown that small quantities of systemically administered leucovorin enter CSF primarily as 5-methyltetrahydrofolate and, in humans, remain 1 to 3 orders of magnitude lower than usual methotrexate concentrations following intrathecal administration. However, high doses of leucovorin may reduce the efficacy of intrathecally administered methotrexate. Leucovorin may enhance the toxicity of fluorouracil (see WARNINGS). | Fluorouracil |  |  | CT |  | Increased toxicity |  | toxicities were found to be reversible with appropriate modification of 5FU administration
Drug Interactions Folic acid in large amounts may counteract the antiepileptic effect of phenobarbital, phenytoin and primidone, and increase the frequency of seizures in susceptible children. Preliminary animal and human studies have shown that small quantities of systemically administered leucovorin enter CSF primarily as 5-methyltetrahydrofolate and, in humans, remain 1 to 3 orders of magnitude lower than usual methotrexate concentrations following intrathecal administration. However, high doses of leucovorin may reduce the efficacy of intrathecally administered methotrexate. Leucovorin may enhance the toxicity of fluorouracil (see WARNINGS). | Legend: C = Case Study; CT = Clinical Trial; T = Theoretical Drug-Food Interactions Interactions with food have not been established. Drug-Herb Interactions Interactions with herbal products have not been established. Drug-Laboratory Test Interactions Interactions with laboratory tests have not been established.
Fertility, Pregnancy, & Lactation / Special populations
Pregnancy Teratogenic Effects Pregnancy Category C Animal reproduction studies have not been conducted with leucovorin. It is also not known whether leucovorin can cause fetal harm when administered to a pregnant woman or can affect reproduction capacity. Leucovorin should be given to a pregnant woman only if clearly needed. Nursing Mothers It is not known whether this drug is excreted in human milk. Because many drugs are excreted in human milk, caution should be exercised when leucovorin is administered to a nursing mother. Pediatric Use See Drug Interactions subsection. | Special Populations Pregnant Women There are no adequate and well-controlled clinical studies conducted in pregnant or breast-feeding women. Animal studies do not indicate reproductive toxicity (see 16 Non-clinical toxicology). There are no indications that folic acid induces harmful effects if administered during pregnancy. During pregnancy, 5-fluorouracil and methotrexate should only be administered on strict indications, where the benefits of the drug to the mother should be weighed against possible hazards to the foetus. Should treatment with methotrexate or other folate antagonists take place despite pregnancy or lactation, there are no limitations as to the use of LEDERLE LEUCOVORIN (calcium folinate) to diminish toxicity or counteract the effects. 5-fluorouracil use is generally contraindicated during pregnancy and contraindicated during breast-feeding; this applies also to the combined use of LEDERLE LEUCOVORIN (calcium folinate) with 5-fluorouracil. Please refer also to the health-care professional label for methotrexate, other folate antagonists and 5-fluorouracil-containing medicinal products. Breast-feeding It is not known whether this drug is excreted in human milk. Because many drugs are excreted in human milk, caution should be exercised when LEDERLE LEUCOVORIN is administered to a nursing mother. Pediatrics Pediatrics (< 18 years of age): No data are available to Health Canada; therefore, Health Canada has not authorized an indication for pediatric use. Geriatrics Geriatrics: Evidence from clinical studies and experience suggests that use in the geriatric population is associated with differences in safety or effectiveness (WARNINGS AND PRECAUTIONS, General). Deaths from severe enterocolitis, diarrhea and dehydration have been reported in elderly patients receiving leucovorin and fluorouracil. Concomitant granulocytopenia and fever were present in some but not all of the patients. NON-CLINICAL TOXICOLOGY Genotoxicity, carcinogenicity, and fertility studies have not been conducted with calcium folinate. Embryo-fetal reproduction toxicity studies have been performed in rats and rabbits. Rats were dosed up to 1800 mg/m^2 which is 9 times the maximum recommended human dose, and rabbits were dosed up to 3300 mg/m^2 which is 16 times the maximum recommended human dose. There was no embryo-fetal toxicity noted in rabbits. At the maximum dose in rats, there was a slight increase in early embryonic resorptions and no other adverse effects on embryo-fetal development. No resorptions were noted in dose groups at 5 times the maximum recommended human dose.
Adverse reactions
ADVERSE REACTIONS Allergic sensitization, including anaphylactoid reactions and urticaria, has been reported following the administration of both oral and parenteral leucovorin. To report SUSPECTED ADVERSE REACTIONS, contact Teva at 1-888-838-2872 or FDA at 1-800-FDA-1088 or www.fda.gov/medwatch. | Adverse Reactions Adverse Reaction Overview Allergic sensitization, including anaphylactoid/anaphylactic reactions (including shock) and urticaria, has been reported following administration of LEDERLE LEUCOVORIN. Table 3 – Adverse Reactions associated with LEDERLE LEUCOVORIN
ADVERSE REACTIONS Allergic sensitization, including anaphylactoid reactions and urticaria, has been reported following the administration of both oral and parenteral leucovorin. To report SUSPECTED ADVERSE REACTIONS, contact Teva at 1-888-838-2872 or FDA at 1-800-FDA-1088 or www.fda.gov/medwatch. | System Organ Class |  |  |  |  | Adverse Reaction
ADVERSE REACTIONS Allergic sensitization, including anaphylactoid reactions and urticaria, has been reported following the administration of both oral and parenteral leucovorin. To report SUSPECTED ADVERSE REACTIONS, contact Teva at 1-888-838-2872 or FDA at 1-800-FDA-1088 or www.fda.gov/medwatch. | Immune system disorders
ADVERSE REACTIONS Allergic sensitization, including anaphylactoid reactions and urticaria, has been reported following the administration of both oral and parenteral leucovorin. To report SUSPECTED ADVERSE REACTIONS, contact Teva at 1-888-838-2872 or FDA at 1-800-FDA-1088 or www.fda.gov/medwatch. | Frequency undetermined |  |  |  |  | Allergic reactions, urticarial
ADVERSE REACTIONS Allergic sensitization, including anaphylactoid reactions and urticaria, has been reported following the administration of both oral and parenteral leucovorin. To report SUSPECTED ADVERSE REACTIONS, contact Teva at 1-888-838-2872 or FDA at 1-800-FDA-1088 or www.fda.gov/medwatch. | Very Rare |  |  |  |  | Anaphylactoid/ anaphylactoid reactions (including shock)
ADVERSE REACTIONS Allergic sensitization, including anaphylactoid reactions and urticaria, has been reported following the administration of both oral and parenteral leucovorin. To report SUSPECTED ADVERSE REACTIONS, contact Teva at 1-888-838-2872 or FDA at 1-800-FDA-1088 or www.fda.gov/medwatch. | Nervous System disorders
ADVERSE REACTIONS Allergic sensitization, including anaphylactoid reactions and urticaria, has been reported following the administration of both oral and parenteral leucovorin. To report SUSPECTED ADVERSE REACTIONS, contact Teva at 1-888-838-2872 or FDA at 1-800-FDA-1088 or www.fda.gov/medwatch. | Rare |  |  |  |  | Seizures and/or syncope
ADVERSE REACTIONS Allergic sensitization, including anaphylactoid reactions and urticaria, has been reported following the administration of both oral and parenteral leucovorin. To report SUSPECTED ADVERSE REACTIONS, contact Teva at 1-888-838-2872 or FDA at 1-800-FDA-1088 or www.fda.gov/medwatch. | General disorders and administration site conditions
ADVERSE REACTIONS Allergic sensitization, including anaphylactoid reactions and urticaria, has been reported following the administration of both oral and parenteral leucovorin. To report SUSPECTED ADVERSE REACTIONS, contact Teva at 1-888-838-2872 or FDA at 1-800-FDA-1088 or www.fda.gov/medwatch. | Frequency undetermined |  |  |  |  | Fever
ADVERSE REACTIONS Allergic sensitization, including anaphylactoid reactions and urticaria, has been reported following the administration of both oral and parenteral leucovorin. To report SUSPECTED ADVERSE REACTIONS, contact Teva at 1-888-838-2872 or FDA at 1-800-FDA-1088 or www.fda.gov/medwatch. | Clinical Trial Adverse Reactions Clinical trials are conducted under very specific conditions. The adverse reaction rates observed in the clinical trials; therefore, may not reflect the rates observed in practice and should not be compared to the rates in the clinical trials of another drug. Adverse reaction information from clinical trials may be useful in identifying and approximating rates of adverse drug reactions in real-world use. LEDERLE LEUCOVORIN in Combination with 5-fluorouracil (5-FU) In combination regimens, the toxicity profile of 5FU is enhanced by LEDERLE LEUCOVORIN. The most common manifestations are mucositis, stomatitis, leukopenia and/or diarrhea, which may be dose-limiting. In clinical trials with this drug combination, these toxicities were found to be reversible with appropriate modification of 5FU administration. Generally, the safety profile depends on the applied regimen of 5-fluorouracil due to enhancement of the 5- fluorouracil induced toxicities. Additional undesirable effects when used in combination with 5-fluorouracil: Table 4 – Adverse Reactions associated with LEDERLE LEUCOVORIN in Combination with 5-FU
 | System Organ Class |  |  |  |  | Adverse Reaction
 | Gastrointestinal disorders
 | Very common |  |  |  |  | Nausea and Vomiting, diarrhea
 | Hepatobiliary disorders
 | Frequency undetermined |  |  |  |  | Hyperammonemia
 | Skin and subcutaneous tissue disorders
 | Common |  |  |  |  | Palmar-Plantar Erythrodysaesthesia
 | General disorders and administration site conditions
 | Very common |  |  |  |  | Mucositis, including stomatitis and chelitis
 | Post-Market Adverse Reactions Cases of Stevens-Johnson Syndrome (SJS) and Toxic Epidermal Necrolysis (TEN), some fatal, have been reported in patients receiving calcium folinate in combination with other agents known to be associated with these disorders. A contributory role of leucovorin in these occurrences of SJS/TEN cannot be excluded. Fatalities have occurred as a result of gastrointestinal toxicity (predominantly mucositis and diarrhea) and myelosuppression. In patients with diarrhea, rapid clinical deterioration leading to death can occur.
Overdosage
OVERDOSAGE Excessive amounts of leucovorin may nullify the chemotherapeutic effect of folic acid antagonists. | Overdose Overdosage Folic acid is a water-soluble vitamin converted in the body by the action of folate reductase to folinic acid (calcium folinate), which is rapidly eliminated in the urine. Folic acid has low acute and chronic toxicity in humans. There have been no reported sequelae in patients who have received significantly more calcium folinate than the recommended dosage. However, excessive amounts of calcium folinate may nullify the chemotherapeutic effect of folic acid antagonists. No adverse effects have been noted in adults after the ingestion of 400 mg/day for 5 months or 10 mg/day for 5 years. Should overdosage of the combination of 5-fluorouracil and calcium folinate occur, the overdosage instructions for 5-FU should be followed.
 |  |  | For management of a suspected drug overdose, contact your regional poison control centre.
Dosage and administration
DOSAGE AND ADMINISTRATION Leucovorin calcium tablets are intended for oral administration. Because absorption is saturable, oral administration of doses greater than 25 mg is not recommended. Impaired Methotrexate Elimination or Inadvertent Overdosage Leucovorin rescue should begin as soon as possible after an inadvertent overdosage and within 24 hours of methotrexate administration when there is delayed excretion (see WARNINGS). Leucovorin 15 mg (10 mg/m^2) should be administered IM, IV, or PO every 6 hours until serum methotrexate level is less than 10 ^-8 M. In the presence of gastrointestinal toxicity, nausea, or vomiting, leucovorin should be administered parenterally. Serum creatinine and methotrexate levels should be determined at 24-hour intervals. If the 24-hour serum creatinine has increased 50% over baseline or if the 24-hour methotrexate level is greater than 5 x 10 ^-6 M or the 48 hour level is greater than 9 x 10 ^-7 M, the dose of leucovorin should be increased to 150 mg (100 mg/m^2) IV every 3 hours until the methotrexate level is less than 10 ^-8 M. Doses greater than 25 mg should be given parenterally (see CLINICAL PHARMACOLOGY). Hydration (3 L/d) and urinary alkalinization with sodium bicarbonate should be employed concomitantly. The bicarbonate dose should be adjusted to maintain the urine pH at 7 or greater. The recommended dose of leucovorin to counteract hematologic toxicity from folic acid antagonists with less affinity for mammalian dihydrofolate reductase than methotrexate (i.e., trimethoprim, pyrimethamine) is substantially less, and 5 to 15 mg of leucovorin per day has been recommended by some investigators. Patients who experience delayed early methotrexate elimination are likely to develop reversible non-oliguric renal failure. In addition to appropriate leucovorin therapy, these patients require continuing hydration and urinary alkalinization, and close monitoring of fluid and electrolyte status, until the serum methotrexate level has fallen to below 0.05 micromolar and the renal failure has resolved. Some patients will have abnormalities in methotrexate elimination or renal function following methotrexate administration, which are significant but less severe. These abnormalities may or may not be associated with significant clinical toxicity. If significant clinical toxicity is observed, leucovorin rescue should be extended for an additional 24 hours (total 14 doses over 84 hours) in subsequent courses of therapy. The possibility that the patient is taking other medications which interact with methotrexate (e.g., medications which may interfere with methotrexate elimination or binding to serum albumin) should always be reconsidered when laboratory abnormalities or clinical toxicities are observed. | Dosage & Administration Recommended Dose and Dosage Adjustment Impaired methotrexate Elimination or Accidental Overdosage: LEDERLE LEUCOVORIN rescue should begin as soon as possible after an inadvertent overdosage and within 24 hours of methotrexate administration when there is delayed excretion (WARNINGS AND PRECAUTIONS). As the time interval between the administration of antifolate and LEDERLE LEUCOVORIN rescue increases, the effectiveness of LEDERLE LEUCOVORIN in counteracting toxicity decreases. There are no fixed guidelines regarding the dose of methotrexate that triggers an automatic subsequent calcium folinate administration, since tolerance to this folate antagonist depends on various factors. The dose of methotrexate varies, nevertheless folinate rescue is necessary when methotrexate is given at doses exceeding 500 mg/m^2 and has to be considered with doses of 100 mg - 500 mg/m^2. Calcium folinate rescue treatment should commence approximately 24 hours after the beginning of methotrexate infusion. Dosage regimens vary depending upon the dose of methotrexate administered. In general, calcium folinate should be administered at a dose of 15 mg (approximately 10 mg/m^2) every 6 hours for 10 doses, either parenterally by intramuscular injection, bolus intravenous injection, intravenous infusion, or orally using calcium folinate tablets. Monitoring of the serum methotrexate (MTX) concentration is essential in determining the optimal dose and duration of therapy. If serum creatinine increases after methotrexate therapy or if methotrexate plasma concentrations are above certain threshold (see Table 1), the dose of calcium folinate should be increased according to the plasma methotrexate concentrations as soon as the risk is recognized. In the presence of gastrointestinal toxicity, nausea, or vomiting, calcium folinate should be administered parenterally. In the case of intravenous administration, no more than 160 mg of calcium folinate should be injected per minute due to the calcium content of the solution. Further, oral administration of doses greater than 25 mg is not recommended since the digestive absorption of calcium folinate is saturable; these doses should be administered parenterally. In addition to calcium folinate administration, measures to ensure the prompt excretion of methotrexate are an integral part of the calcium folinate rescue treatment. These measures include:; a) Maintenance of urine output above 2,500 mL/24 hr in adults by increased oral or intravenous fluids 12 hours before and for 36 hours after the end of methotrexate infusion. b) Alkalinisation of urine so that the urinary pH is greater than 7.0 before methotrexate infusion.; Foods, drinks and drugs that may increase urinary acidity should be avoided during the therapy. c) Plasma methotrexate concentration and serum creatinine should be measured at least 24, 48, and 72 hours after the initiation of the methotrexate infusion. These measurements must be continued until the plasma methotrexate level is less than 5 x 10^-8 molar. (0.05 μm).; Delayed methotrexate excretion may be seen in some patients. This may be caused by a third space accumulation (as seen in ascites or pleural effusion for example), renal insufficiency or inadequate hydration (see WARNINGS AND PRECAUTIONS). Under such circumstances, higher doses of calcium folinate and/or prolonged administration may be indicated. Some dosage and administration guidelines are given in Table 1. Table 1: Dosage and Administration Guidelines for Calcium Folinate Rescue
DOSAGE AND ADMINISTRATION Leucovorin calcium tablets are intended for oral administration. Because absorption is saturable, oral administration of doses greater than 25 mg is not recommended. Impaired Methotrexate Elimination or Inadvertent Overdosage Leucovorin rescue should begin as soon as possible after an inadvertent overdosage and within 24 hours of methotrexate administration when there is delayed excretion (see WARNINGS). Leucovorin 15 mg (10 mg/m^2) should be administered IM, IV, or PO every 6 hours until serum methotrexate level is less than 10 ^-8 M. In the presence of gastrointestinal toxicity, nausea, or vomiting, leucovorin should be administered parenterally. Serum creatinine and methotrexate levels should be determined at 24-hour intervals. If the 24-hour serum creatinine has increased 50% over baseline or if the 24-hour methotrexate level is greater than 5 x 10 ^-6 M or the 48 hour level is greater than 9 x 10 ^-7 M, the dose of leucovorin should be increased to 150 mg (100 mg/m^2) IV every 3 hours until the methotrexate level is less than 10 ^-8 M. Doses greater than 25 mg should be given parenterally (see CLINICAL PHARMACOLOGY). Hydration (3 L/d) and urinary alkalinization with sodium bicarbonate should be employed concomitantly. The bicarbonate dose should be adjusted to maintain the urine pH at 7 or greater. The recommended dose of leucovorin to counteract hematologic toxicity from folic acid antagonists with less affinity for mammalian dihydrofolate reductase than methotrexate (i.e., trimethoprim, pyrimethamine) is substantially less, and 5 to 15 mg of leucovorin per day has been recommended by some investigators. Patients who experience delayed early methotrexate elimination are likely to develop reversible non-oliguric renal failure. In addition to appropriate leucovorin therapy, these patients require continuing hydration and urinary alkalinization, and close monitoring of fluid and electrolyte status, until the serum methotrexate level has fallen to below 0.05 micromolar and the renal failure has resolved. Some patients will have abnormalities in methotrexate elimination or renal function following methotrexate administration, which are significant but less severe. These abnormalities may or may not be associated with significant clinical toxicity. If significant clinical toxicity is observed, leucovorin rescue should be extended for an additional 24 hours (total 14 doses over 84 hours) in subsequent courses of therapy. The possibility that the patient is taking other medications which interact with methotrexate (e.g., medications which may interfere with methotrexate elimination or binding to serum albumin) should always be reconsidered when laboratory abnormalities or clinical toxicities are observed. | Clinical situation |  |  |  | Laboratory findings |  | Calcium folinate dosage and duration
DOSAGE AND ADMINISTRATION Leucovorin calcium tablets are intended for oral administration. Because absorption is saturable, oral administration of doses greater than 25 mg is not recommended. Impaired Methotrexate Elimination or Inadvertent Overdosage Leucovorin rescue should begin as soon as possible after an inadvertent overdosage and within 24 hours of methotrexate administration when there is delayed excretion (see WARNINGS). Leucovorin 15 mg (10 mg/m^2) should be administered IM, IV, or PO every 6 hours until serum methotrexate level is less than 10 ^-8 M. In the presence of gastrointestinal toxicity, nausea, or vomiting, leucovorin should be administered parenterally. Serum creatinine and methotrexate levels should be determined at 24-hour intervals. If the 24-hour serum creatinine has increased 50% over baseline or if the 24-hour methotrexate level is greater than 5 x 10 ^-6 M or the 48 hour level is greater than 9 x 10 ^-7 M, the dose of leucovorin should be increased to 150 mg (100 mg/m^2) IV every 3 hours until the methotrexate level is less than 10 ^-8 M. Doses greater than 25 mg should be given parenterally (see CLINICAL PHARMACOLOGY). Hydration (3 L/d) and urinary alkalinization with sodium bicarbonate should be employed concomitantly. The bicarbonate dose should be adjusted to maintain the urine pH at 7 or greater. The recommended dose of leucovorin to counteract hematologic toxicity from folic acid antagonists with less affinity for mammalian dihydrofolate reductase than methotrexate (i.e., trimethoprim, pyrimethamine) is substantially less, and 5 to 15 mg of leucovorin per day has been recommended by some investigators. Patients who experience delayed early methotrexate elimination are likely to develop reversible non-oliguric renal failure. In addition to appropriate leucovorin therapy, these patients require continuing hydration and urinary alkalinization, and close monitoring of fluid and electrolyte status, until the serum methotrexate level has fallen to below 0.05 micromolar and the renal failure has resolved. Some patients will have abnormalities in methotrexate elimination or renal function following methotrexate administration, which are significant but less severe. These abnormalities may or may not be associated with significant clinical toxicity. If significant clinical toxicity is observed, leucovorin rescue should be extended for an additional 24 hours (total 14 doses over 84 hours) in subsequent courses of therapy. The possibility that the patient is taking other medications which interact with methotrexate (e.g., medications which may interfere with methotrexate elimination or binding to serum albumin) should always be reconsidered when laboratory abnormalities or clinical toxicities are observed. | Normal methotrexate Elimination |  |  |  | Serum methotrexate level ≤ 10 μM at 24 hours after administration, ≤ 1 μM at 48 hours, and < 0.1 μM at 72 hours. |  | 15 mg PO, IM, or IV every 6 hours for 60 hours (10 doses starting at 24 hours after start of methotrexate infusion).
DOSAGE AND ADMINISTRATION Leucovorin calcium tablets are intended for oral administration. Because absorption is saturable, oral administration of doses greater than 25 mg is not recommended. Impaired Methotrexate Elimination or Inadvertent Overdosage Leucovorin rescue should begin as soon as possible after an inadvertent overdosage and within 24 hours of methotrexate administration when there is delayed excretion (see WARNINGS). Leucovorin 15 mg (10 mg/m^2) should be administered IM, IV, or PO every 6 hours until serum methotrexate level is less than 10 ^-8 M. In the presence of gastrointestinal toxicity, nausea, or vomiting, leucovorin should be administered parenterally. Serum creatinine and methotrexate levels should be determined at 24-hour intervals. If the 24-hour serum creatinine has increased 50% over baseline or if the 24-hour methotrexate level is greater than 5 x 10 ^-6 M or the 48 hour level is greater than 9 x 10 ^-7 M, the dose of leucovorin should be increased to 150 mg (100 mg/m^2) IV every 3 hours until the methotrexate level is less than 10 ^-8 M. Doses greater than 25 mg should be given parenterally (see CLINICAL PHARMACOLOGY). Hydration (3 L/d) and urinary alkalinization with sodium bicarbonate should be employed concomitantly. The bicarbonate dose should be adjusted to maintain the urine pH at 7 or greater. The recommended dose of leucovorin to counteract hematologic toxicity from folic acid antagonists with less affinity for mammalian dihydrofolate reductase than methotrexate (i.e., trimethoprim, pyrimethamine) is substantially less, and 5 to 15 mg of leucovorin per day has been recommended by some investigators. Patients who experience delayed early methotrexate elimination are likely to develop reversible non-oliguric renal failure. In addition to appropriate leucovorin therapy, these patients require continuing hydration and urinary alkalinization, and close monitoring of fluid and electrolyte status, until the serum methotrexate level has fallen to below 0.05 micromolar and the renal failure has resolved. Some patients will have abnormalities in methotrexate elimination or renal function following methotrexate administration, which are significant but less severe. These abnormalities may or may not be associated with significant clinical toxicity. If significant clinical toxicity is observed, leucovorin rescue should be extended for an additional 24 hours (total 14 doses over 84 hours) in subsequent courses of therapy. The possibility that the patient is taking other medications which interact with methotrexate (e.g., medications which may interfere with methotrexate elimination or binding to serum albumin) should always be reconsidered when laboratory abnormalities or clinical toxicities are observed. | Delayed late methotrexate elimination |  |  |  | Serum methotrexate level remaining > 0.1 μM at 72 hours, and > 0.1 μM at 96 hours after administration. |  | Continue 15 mg PO, IM, or IV every 6 hours, until methotrexate level is less than 0.1 μM.
DOSAGE AND ADMINISTRATION Leucovorin calcium tablets are intended for oral administration. Because absorption is saturable, oral administration of doses greater than 25 mg is not recommended. Impaired Methotrexate Elimination or Inadvertent Overdosage Leucovorin rescue should begin as soon as possible after an inadvertent overdosage and within 24 hours of methotrexate administration when there is delayed excretion (see WARNINGS). Leucovorin 15 mg (10 mg/m^2) should be administered IM, IV, or PO every 6 hours until serum methotrexate level is less than 10 ^-8 M. In the presence of gastrointestinal toxicity, nausea, or vomiting, leucovorin should be administered parenterally. Serum creatinine and methotrexate levels should be determined at 24-hour intervals. If the 24-hour serum creatinine has increased 50% over baseline or if the 24-hour methotrexate level is greater than 5 x 10 ^-6 M or the 48 hour level is greater than 9 x 10 ^-7 M, the dose of leucovorin should be increased to 150 mg (100 mg/m^2) IV every 3 hours until the methotrexate level is less than 10 ^-8 M. Doses greater than 25 mg should be given parenterally (see CLINICAL PHARMACOLOGY). Hydration (3 L/d) and urinary alkalinization with sodium bicarbonate should be employed concomitantly. The bicarbonate dose should be adjusted to maintain the urine pH at 7 or greater. The recommended dose of leucovorin to counteract hematologic toxicity from folic acid antagonists with less affinity for mammalian dihydrofolate reductase than methotrexate (i.e., trimethoprim, pyrimethamine) is substantially less, and 5 to 15 mg of leucovorin per day has been recommended by some investigators. Patients who experience delayed early methotrexate elimination are likely to develop reversible non-oliguric renal failure. In addition to appropriate leucovorin therapy, these patients require continuing hydration and urinary alkalinization, and close monitoring of fluid and electrolyte status, until the serum methotrexate level has fallen to below 0.05 micromolar and the renal failure has resolved. Some patients will have abnormalities in methotrexate elimination or renal function following methotrexate administration, which are significant but less severe. These abnormalities may or may not be associated with significant clinical toxicity. If significant clinical toxicity is observed, leucovorin rescue should be extended for an additional 24 hours (total 14 doses over 84 hours) in subsequent courses of therapy. The possibility that the patient is taking other medications which interact with methotrexate (e.g., medications which may interfere with methotrexate elimination or binding to serum albumin) should always be reconsidered when laboratory abnormalities or clinical toxicities are observed. | Delayed early methotrexate elimination and/or evidence of acute renal failure |  |  |  | Serum methotrexate level of > 10 μM at 24 hours, or > 1 μM at 48 hours after administration OR a 100% or greater increase in serum creatinine level at 24 hours after methotrexate administration. |  | 150 mg IV every 3 hours, until methotrexate level is less than 1 μM; then 15 mg; IV every 3 hours until methotrexate level is less than 0.1 μM.
DOSAGE AND ADMINISTRATION Leucovorin calcium tablets are intended for oral administration. Because absorption is saturable, oral administration of doses greater than 25 mg is not recommended. Impaired Methotrexate Elimination or Inadvertent Overdosage Leucovorin rescue should begin as soon as possible after an inadvertent overdosage and within 24 hours of methotrexate administration when there is delayed excretion (see WARNINGS). Leucovorin 15 mg (10 mg/m^2) should be administered IM, IV, or PO every 6 hours until serum methotrexate level is less than 10 ^-8 M. In the presence of gastrointestinal toxicity, nausea, or vomiting, leucovorin should be administered parenterally. Serum creatinine and methotrexate levels should be determined at 24-hour intervals. If the 24-hour serum creatinine has increased 50% over baseline or if the 24-hour methotrexate level is greater than 5 x 10 ^-6 M or the 48 hour level is greater than 9 x 10 ^-7 M, the dose of leucovorin should be increased to 150 mg (100 mg/m^2) IV every 3 hours until the methotrexate level is less than 10 ^-8 M. Doses greater than 25 mg should be given parenterally (see CLINICAL PHARMACOLOGY). Hydration (3 L/d) and urinary alkalinization with sodium bicarbonate should be employed concomitantly. The bicarbonate dose should be adjusted to maintain the urine pH at 7 or greater. The recommended dose of leucovorin to counteract hematologic toxicity from folic acid antagonists with less affinity for mammalian dihydrofolate reductase than methotrexate (i.e., trimethoprim, pyrimethamine) is substantially less, and 5 to 15 mg of leucovorin per day has been recommended by some investigators. Patients who experience delayed early methotrexate elimination are likely to develop reversible non-oliguric renal failure. In addition to appropriate leucovorin therapy, these patients require continuing hydration and urinary alkalinization, and close monitoring of fluid and electrolyte status, until the serum methotrexate level has fallen to below 0.05 micromolar and the renal failure has resolved. Some patients will have abnormalities in methotrexate elimination or renal function following methotrexate administration, which are significant but less severe. These abnormalities may or may not be associated with significant clinical toxicity. If significant clinical toxicity is observed, leucovorin rescue should be extended for an additional 24 hours (total 14 doses over 84 hours) in subsequent courses of therapy. The possibility that the patient is taking other medications which interact with methotrexate (e.g., medications which may interfere with methotrexate elimination or binding to serum albumin) should always be reconsidered when laboratory abnormalities or clinical toxicities are observed. | Hydration (3 L/d) and urinary alkalinization with NaHCO3 should be employed concomitantly. The bicarbonate dose should be adjusted to maintain the urine pH at 7.0 or greater. Megaloblastic Anemia Due to Folic Acid Deficiency: Doses up to 15 mg daily have been suggested. Health Canada has not authorized an indication for pediatric use. Administration Tablets are administered orally.
How supplied/Composition & form/Storage and handling/References
HOW SUPPLIED Leucovorin calcium tablets USP, 5 mg are available as white, round, biconvex tablets, debossed with "stylized b" on one side and 484 on the other side, packaged in bottles of 30 (NDC 0555-0484-01) and 100 (NDC 0555-0484-02) tablets. Leucovorin calcium tablets USP, 25 mg are available as pale green, round, biconvex tablets, debossed with "stylized b" on one side and 485 on the other side, packaged in bottles of 25 (NDC 0555-0485-27) tablets.; REFERENCES; 1. Grem JL, Shoemaker DD, Petrelli NJ, Douglas HO. Severe and fatal toxic effects observed in treatment with high- and low-dose leucovorin plus 5-fluorouracil for colorectal carcinoma. Cancer Treat Rep 1987;71:1122. 2. Link MP, Goorin AM, Miser AW et al. The effect of adjuvant chemotherapy on relapse-free survival in patients with osteosarcoma of the extremity. N Engl J Med 1986;314:1600-1606. | Composition & Form Dosage Forms Composition And Packaging Table 2 – Dosage Forms, Strengths, Composition and Packaging
HOW SUPPLIED Leucovorin calcium tablets USP, 5 mg are available as white, round, biconvex tablets, debossed with "stylized b" on one side and 484 on the other side, packaged in bottles of 30 (NDC 0555-0484-01) and 100 (NDC 0555-0484-02) tablets. Leucovorin calcium tablets USP, 25 mg are available as pale green, round, biconvex tablets, debossed with "stylized b" on one side and 485 on the other side, packaged in bottles of 25 (NDC 0555-0485-27) tablets.; REFERENCES; 1. Grem JL, Shoemaker DD, Petrelli NJ, Douglas HO. Severe and fatal toxic effects observed in treatment with high- and low-dose leucovorin plus 5-fluorouracil for colorectal carcinoma. Cancer Treat Rep 1987;71:1122. 2. Link MP, Goorin AM, Miser AW et al. The effect of adjuvant chemotherapy on relapse-free survival in patients with osteosarcoma of the extremity. N Engl J Med 1986;314:1600-1606. | Route of Administration |  |  |  | Dosage Form / Strength/Composition |  | Non-medicinal Ingredients
HOW SUPPLIED Leucovorin calcium tablets USP, 5 mg are available as white, round, biconvex tablets, debossed with "stylized b" on one side and 484 on the other side, packaged in bottles of 30 (NDC 0555-0484-01) and 100 (NDC 0555-0484-02) tablets. Leucovorin calcium tablets USP, 25 mg are available as pale green, round, biconvex tablets, debossed with "stylized b" on one side and 485 on the other side, packaged in bottles of 25 (NDC 0555-0485-27) tablets.; REFERENCES; 1. Grem JL, Shoemaker DD, Petrelli NJ, Douglas HO. Severe and fatal toxic effects observed in treatment with high- and low-dose leucovorin plus 5-fluorouracil for colorectal carcinoma. Cancer Treat Rep 1987;71:1122. 2. Link MP, Goorin AM, Miser AW et al. The effect of adjuvant chemotherapy on relapse-free survival in patients with osteosarcoma of the extremity. N Engl J Med 1986;314:1600-1606. | Oral |  |  |  | Tablet 5 mg; Each tablet contains 5 mg of folinic acid as calcium folinate |  | Lactose, Magnesium Stearate, Microcrystalline; Cellulose, Sodium Starch Glycolate and Starch; Pregelatinized 1500
HOW SUPPLIED Leucovorin calcium tablets USP, 5 mg are available as white, round, biconvex tablets, debossed with "stylized b" on one side and 484 on the other side, packaged in bottles of 30 (NDC 0555-0484-01) and 100 (NDC 0555-0484-02) tablets. Leucovorin calcium tablets USP, 25 mg are available as pale green, round, biconvex tablets, debossed with "stylized b" on one side and 485 on the other side, packaged in bottles of 25 (NDC 0555-0485-27) tablets.; REFERENCES; 1. Grem JL, Shoemaker DD, Petrelli NJ, Douglas HO. Severe and fatal toxic effects observed in treatment with high- and low-dose leucovorin plus 5-fluorouracil for colorectal carcinoma. Cancer Treat Rep 1987;71:1122. 2. Link MP, Goorin AM, Miser AW et al. The effect of adjuvant chemotherapy on relapse-free survival in patients with osteosarcoma of the extremity. N Engl J Med 1986;314:1600-1606. | Availability: Bottles of 24 tablets Bottles of 100 tablets Storage & Handling Special Handling Instructions There are no special handling instructions for this drug product. Storage And Stability LEDERLE LEUCOVORIN Tablets 5 mg: Tablets should be stored at 15-30°C. Protect from light.
Pharmacokinetics
 | Pharmacokinetics The pharmacokinetics after intravenous, intramuscular and oral administration of a 25 mg dose of calcium folinate were studied in male volunteers. After intravenous administration, serum total reduced folates (as measured by Lactobacillus casei assay) reached a mean peak of 1259 ng/mL (range 897-1625). The mean time to peak was 10 minutes. This initial rise in total reduced folates was primarily due to the parent compound 5-formyl-THF (measured by Streptococcus faecalis assay), which rose to 1206 ng/mL at 10 minutes. A sharp drop in parent compound followed and coincided with the appearance of the metabolite (also active), 5-methyl-THF, which became the predominant circulating form of the drug. The mean peak of 5-methyl-THF was 258 ng/mL and occurred at 1.3 hours. The terminal half-life for total reduced folates was 6.2 hours. After intramuscular injection, the mean peak of serum total reduced folates was 436 ng/mL (range 240-725) and occurred at 52 minutes. Similar to IV administration, the initial sharp rise was due to the parent compound. The mean peak of 5-formyl-THF was 360 ng/mL and occurred at 28 minutes. The level of the metabolite 5-methyl-THF increased subsequently over time until at 1.5 hours it represented 50% of the circulating total folates. The mean peak of 5-methyl-THF was 226 ng/mL at 2.8 hours. The terminal half-life of total reduced folates was 6.2 hours. There was no difference of statistical significance between IM and IV administration in the AUC for total reduced folates, 5-formyl-THF or 5-methyl-THF. After oral administration of calcium folinate reconstituted with the aromatic elixir, the mean peak concentration of serum total reduced folates was 393 ng/mL (range 160-550). The mean time to peak was 2.3 hours and the terminal half-life was 5.7 hours. The major component was the metabolite 5-methyltetrahydrofolate to which calcium folinate is partially converted in the intestinal mucosa. The mean peak of 5-methyl-THF was 367 ng/mL at 2.4 hours. The peak level of the parent compound was 51 ng/mL at 1.2 hours. The AUC of total reduced folates after oral administration of the 25 mg dose was 92% of the AUC after intravenous administration. Following oral administration, calcium folinate is rapidly absorbed and enters the general body pool of reduced folates. Folate is concentrated in the liver and cerebrospinal fluid although distribution occurs to all body tissues. Folates are mainly excreted in the urine, with small amounts in the faeces. Parenteral administration of calcium folinate gives higher peak plasma levels than oral administration, but the total plasma folate pool of folinic acid plus its metabolite (N^5methyl—H4-folate) remains unchanged. Oral absorption of calcium folinate is saturable at doses above 25 mg.^36 The apparent bioavailability of calcium folinate was 97% for 25 mg, 75% for 50 mg and 37% for 100 mg. Calcium folinate is the calcium salt of 5-formyl tetrahydrofolic acid. It is an active metabolite of folinic acid and an essential coenzyme of nucleic acid synthesis in cytotoxic chemotherapy. Calcium folinate is frequently used to diminish the toxicity and counteract the action of folate antagonists, such as methotrexate. Calcium folinate and folate antagonists share the same membrane transport carrier and compete for transport into cells, stimulating folate antagonist efflux. It also protects cells from the effect of folate antagonists by repletion of the reduced folate pool. Calcium folinate serves as a pre-reduced source of H4 folate: it can therefore bypass folate antagonist blockage and provide a source for the various coenzyme forms of folic acid. Calcium folinate is also frequently used in the biochemical modulation of fluoropyridine (5-FU) to enhance its cytotoxic activity. 5-FU inhibits thymidylate synthase (TS), a key enzyme involved in pyrimidine biosynthesis, and calcium folinate enhances TS inhibition by increasing the intracellular folate pool, thus stabilizing the 5-FU-TS complex and increasing 5-FU activity. A folic acid deficiency is produced during therapy with the folic acid antagonists, aminopterin and amethopterin (methotrexate), used as antineoplastic agents and with the chemotherapeutic agent, pyrimethamine. These agents competitively inhibit the conversion of folic acid to folinic acid. Their affinity for folate reductase is so much greater than that of folic acid that not even large doses of folic acid will correct the drug-induced deficiency. In the event of a severe toxic reaction, the already reduced form, folinic acid, can be given, since it can be used directly to form new coenzyme.

PACKAGE/LABEL PRINCIPAL DISPLAY PANEL – 24 count bottle label

DIN 02170493

PrLEDERLE
LEUCOVORIN®/MD
Calcium folinate tablets USP
Comprimés de folinate de
calcium, USP

5 mg

24 tablets / comprimés

Pfizer

PACKAGE/LABEL PRINCIPAL DISPLAY PANEL – 100 count bottle label

DIN 02170493

PrLEDERLE
LEUCOVORIN®/MD
Calcium folinate tablets USP
Comprimés de folinate de
calcium, USP

5 mg

100 tablets / comprimés

Pfizer